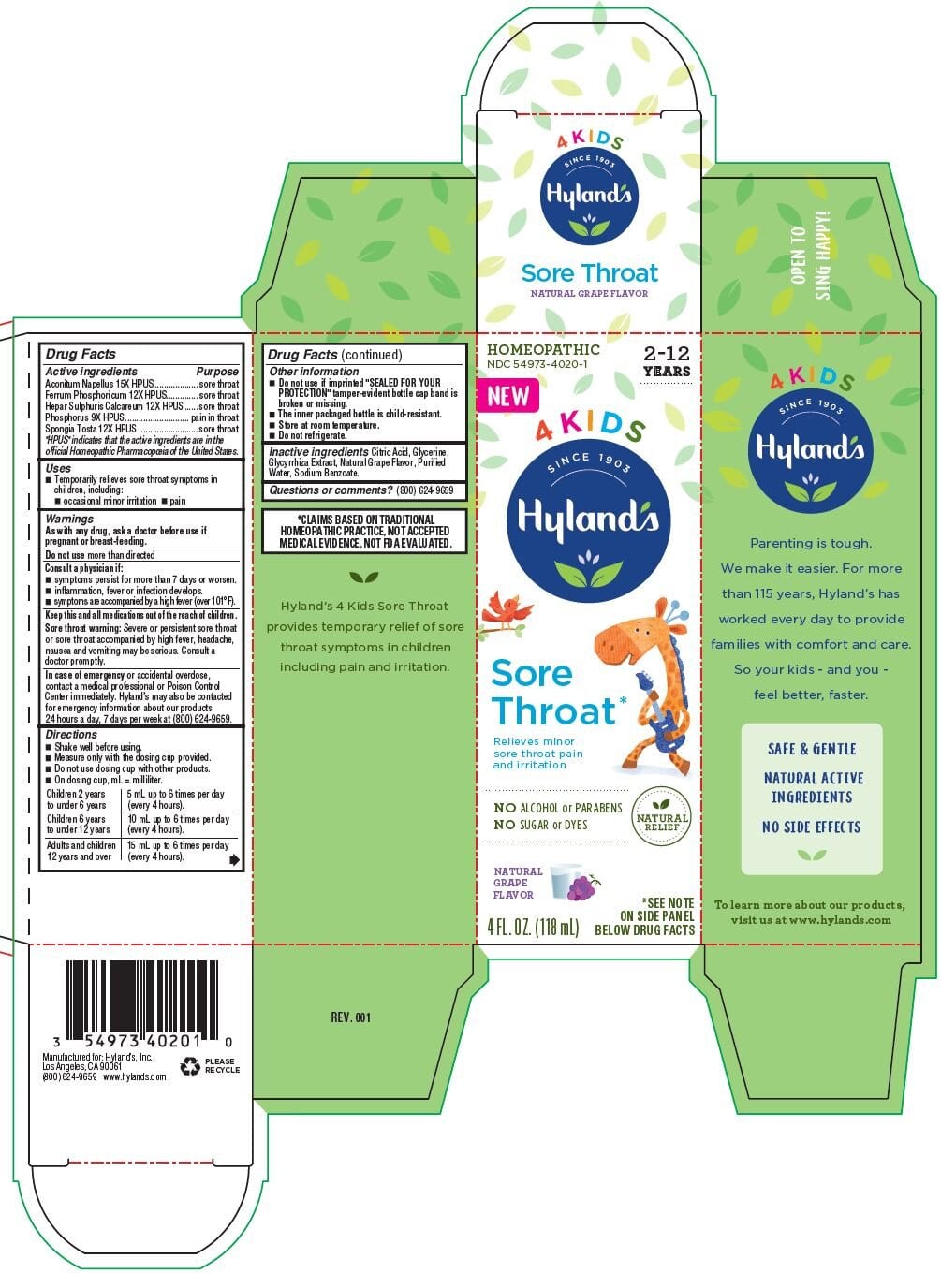 DRUG LABEL: 4 Kids Sore Throat Grape
NDC: 54973-4020 | Form: LIQUID
Manufacturer: Hyland's Inc.
Category: homeopathic | Type: HUMAN OTC DRUG LABEL
Date: 20221123

ACTIVE INGREDIENTS: CALCIUM SULFIDE 12 [hp_X]/1 mL; PHOSPHORUS 9 [hp_X]/1 mL; ACONITUM NAPELLUS 15 [hp_X]/1 mL; SPONGIA OFFICINALIS SKELETON, ROASTED 12 [hp_X]/1 mL; FERROSOFERRIC PHOSPHATE 12 [hp_X]/1 mL
INACTIVE INGREDIENTS: GLYCYRRHIZA GLABRA; SODIUM BENZOATE; WATER; CITRIC ACID MONOHYDRATE; GLYCERIN

Hyland's 4 Kids Sore Throat Grape

Drug Facts

Active ingredients

Aconitum Napellus 15X HPUS

Ferrum Phosphoricum 12X HPUS

Hepar Sulphuris Calcareum 12X HPUS

Phosphorus 9X HPUS

Spongia Tosta 12X HPUS

HPUS" indicates that the active ingredients are in the official Homeopathic Pharmacopoeia of the United States.

Purpose

sore throat

sore throat

sore throat

pain in throat

sore throat

Uses

- Temporarily relieves sore throat symptoms in children, including:
- occasional minor irritation 
- pain

Warnings

As with any drug, ask a doctor before use if pregnant or breast-feeding.

Do not use more than directed

Consult a physician if:

- symptoms persist for more than 7 days or worsen.
- inflammation, fever or infection develops.
- symptoms are accompanied by a high fever (over 101°F).

KEEP OUT OF REACH OF CHILDREN

Keep this and all medications out of the reach of children.

Sore throat warning: Severe or persistent sore throat or sore throat accompanied by high fever, headache, nausea and vomiting may be serious. Consult a doctor promptly.

In case of emergency or accidental overdose, contact a medical professional or Poison Control Center immediately. Hyland’s may also be contacted for emergency information about our products 24 hours a day, 7 days per week at (800) 624-9659.

Directions

- Shake well before using.
- Measure only with the dosing cup provided.
- Do not use dosing cup with other products.
- On dosing cup, mL = milliliter.

Children 2 years; to under 6 years | 5 mL up to 6 times per day (every 4 hours).
Children 6 years; to under 12 years | 10 mL up to 6 times per day (every 4 hours).
Adults and children; 12 years and over | 15 mL up to 6 times per day (every 4 hours).

Other information

- Do not use if imprinted "SEALED FOR YOUR PROTECTION" tamper-evident bottle cap band is broken or missing.
- The inner packaged bottle is child-resistant.
- Store at room temperature.
- Do not refrigerate.

Inactive ingredients

Citric Acid, Glycerine, Glycyrrhiza Extract, Natural Grape Flavor, Purified Water, Sodium Benzoate.

Questions or comments?

(800) 624-9659

*CLAIMS BASED ON TRADITIONAL HOMEOPATHIC PRACTICE, NOT ACCEPTED MEDICAL EVIDENCE. NOT FDA EVALUATED.

Principal Display Panel - 118 mL Bottle Carton

HOMEOPATHIC

NDC 54973-4020-1

2-12

YEARS

NEW

4 KIDS

SINCE 1903

Hyland's

Sore

Throat*

Relieves minor

sore throat pain

and irritation

NO ALCOHOL or PARABENS

NO SUGAR or DYES

NATURAL

RELIEF

NATURAL

GRAPE

FLAVOR

4 FL. OZ (118 mL)

*SEE NOTE

ON SIDE PANEL

BELOW DRUG FACTS